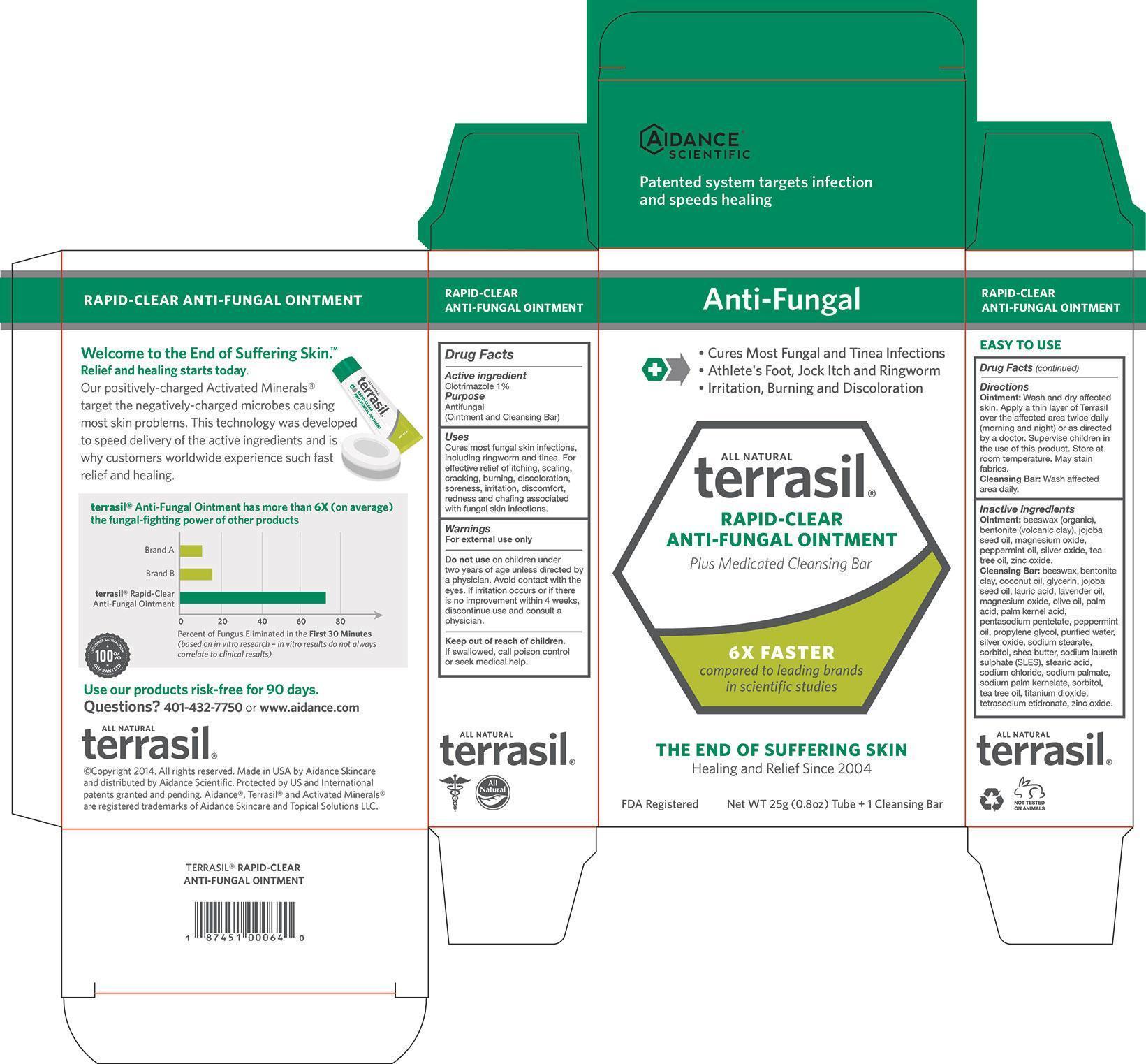 DRUG LABEL: Terrasil Rapid-Clear Anti-Fungal
NDC: 24909-165 | Form: KIT | Route: TOPICAL
Manufacturer: Aidance Skincare & Topical Solutions, LLC
Category: otc | Type: HUMAN OTC DRUG LABEL
Date: 20140418

ACTIVE INGREDIENTS: CLOTRIMAZOLE 1 g/100 g; CLOTRIMAZOLE 1 g/100 g
INACTIVE INGREDIENTS: BENTONITE; JOJOBA OIL; MAGNESIUM OXIDE; PEPPERMINT OIL; SILVER OXIDE; TEA TREE OIL; WHITE WAX; ZINC OXIDE; BENTONITE; COCONUT OIL; GLYCERIN; JOJOBA OIL; LAURIC ACID; LAVENDER OIL; MAGNESIUM OXIDE; OLIVE OIL; PALM ACID; PALM KERNEL ACID; PENTASODIUM PENTETATE; PEPPERMINT OIL; PROPYLENE GLYCOL; SILVER OXIDE; SODIUM STEARATE; SHEA BUTTER; SODIUM LAURETH SULFATE; STEARIC ACID; SODIUM CHLORIDE; SODIUM PALMATE; SODIUM PALM KERNELATE; SORBITOL; TEA TREE OIL; TITANIUM DIOXIDE; ETIDRONATE TETRASODIUM; WATER; WHITE WAX; ZINC OXIDE

Drug Facts

Active Ingredient

Clotrimazole 1%

Purpose

Antifungal

Uses

Cures most fungal skin infections, including ringworm and tinea.
For effective relief of itching, scaling, cracking, burning, discoloration, soreness,
irritation, discomfort, redness and chafing associated with fungal skin infections.

Warnings

For external use only
Do not use on children under two years of age unless directed by a physician.
Avoid contact with the eyes. If irritation occurs or if there is no improvement within 4 weeks,
discontinue use and consult a physician.

Keep out of reach of children.

If swallowed, call poison control or seek medical help.

Directions

Ointment: Wash and dry affected skin.
Apply a thin layer of Terrasil over the affected area twice daily
(morning and night) or as directed by a doctor. Supervise children in the use of this product.
Store at room temperature. May stain fabrics.
Cleansing Bar: Wash affected area daily.

Inactive Ingredients

Ointment: beeswax (organic), bentonite (volcanic clay), jojoba seed oil, magnesium oxide, peppermint oil, silver oxide, tea tree oil, zinc oxide.

Cleansing Bar: beeswax, bentonite clay, coconut oil, glycerin, jojoba seed oil, lauric acid, lavender oil, magnesium oxide, olive oil, palm acid, palm kernel acid, pentasodium pentetate, peppermint oil, propylene glycol, purified water, silver oxide, sodium stearate, sorbitol, shea butter, sodium laureth sulphate (SLES), stearic acid, sodium chloride, sodium palmate, sodium palm kernelate, sorbitol, tea tree oil, titanium dioxide, tetrasodium etidronate, zinc oxide.

PRINCIPAL DISPLAY PANEL - BOX

Anti-Fungal

- Cures Most Fungal and Tinea Infections
- Athlete's Foot, Jock Itch and Ringworm
- Irritation, Burning and Discoloration

All Natural

terrasil

RAPID-CLEAR ANTI-FUNGAL OINTMENT

Plus Medicated Cleansing Bar

6X FASTER

compared to leading brands
in scientific studies

THE END OF SUFFERING SKIN

Healing and Relief Since 2004